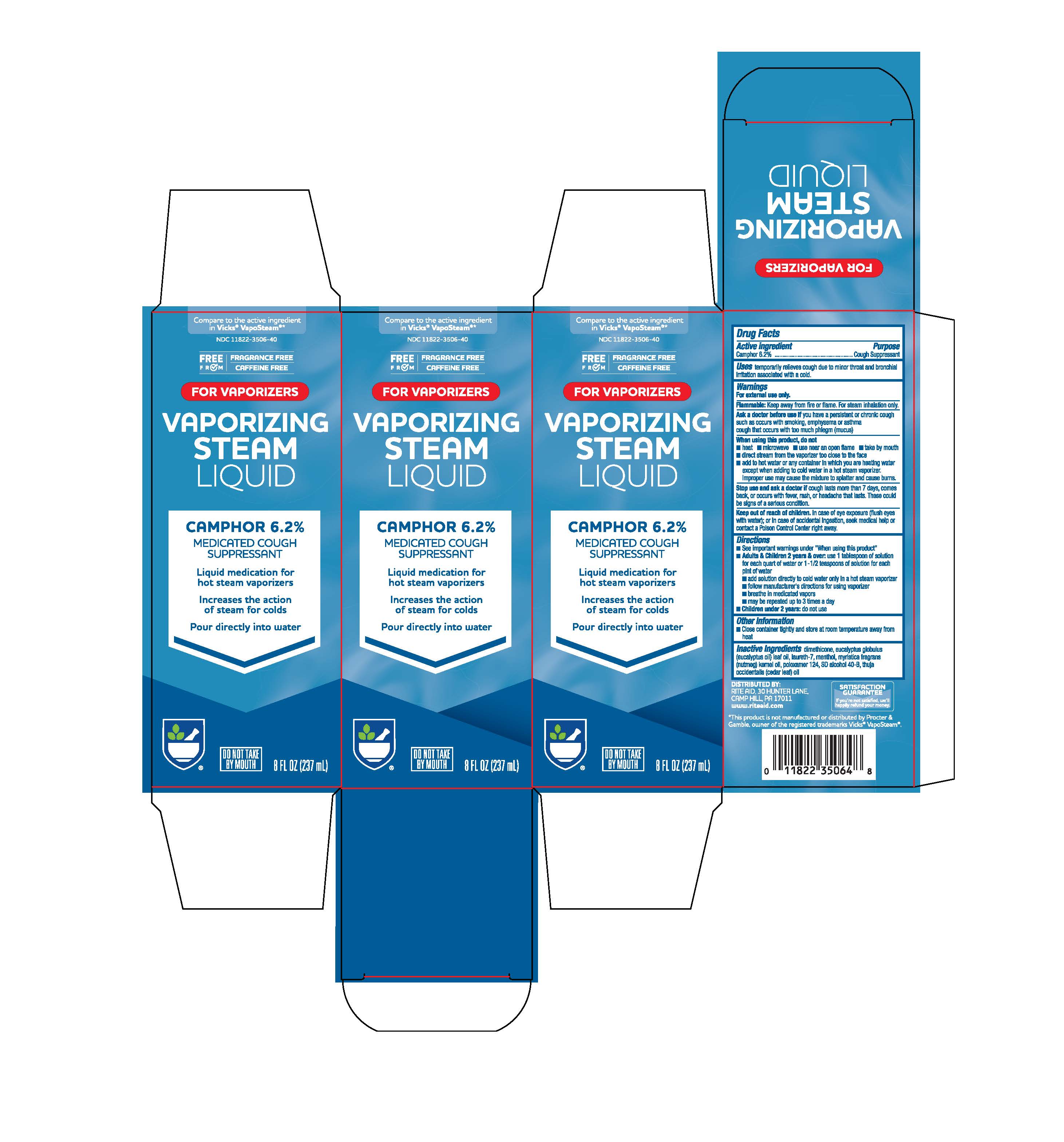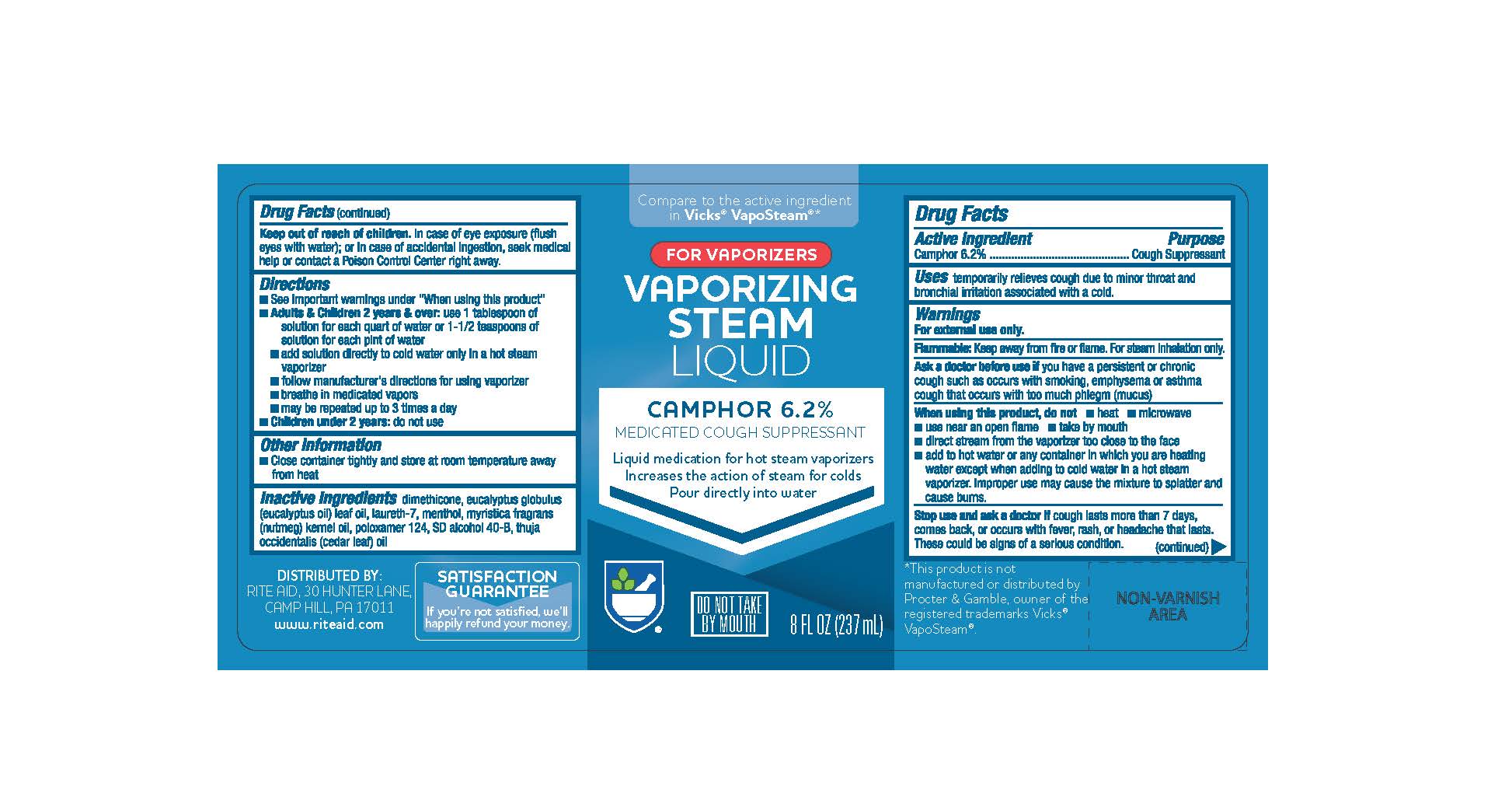 DRUG LABEL: Rite Aid Pharmacy congestion relief vaporizing steam
NDC: 11822-3506 | Form: LIQUID
Manufacturer: Rite Aid Pharmacy
Category: otc | Type: HUMAN OTC DRUG LABEL
Date: 20260114

ACTIVE INGREDIENTS: CAMPHOR (SYNTHETIC) 6.2 g/100 mL
INACTIVE INGREDIENTS: DIMETHICONE; EUCALYPTUS GLOBULUS LEAF; LAURETH-7; MENTHOL; NUTMEG OIL; POLOXAMER 124; ALCOHOL; CEDAR LEAF OIL

Rite-Aid®Vaporizing Steam 8oz

Active Ingredient

Active Ingredient Purpose
Camphor 6.2%.............................Cough Suppressant

Uses

temporarily relieves cough due to minor throat and bronchial irritation associated with a cold.

Warnings

For external use only

Flammable:

Flammable: Keep away from fire or flame. For steam inhalation only.

Ask a doctor before use, if you have a persistant or chronic cough such as occurs with smoking, asthma, emphysema, or if cough is accompanied by excessive phlegm (mucus)

When using this product, do not -heat -microwave

-use near an open flame -take by mouth

-direct stream from the vaporizer too close to the face

-add to hot water or any container in which you are heating water except when adding to cold water in a hot steam vaporizer. Improper use may cause the mixture to splatter and cause burns.

Stop use and ask a doctor if cough lasts more than 7 days, comes back, or occurs with fever, rash, or headache that lasts. These could be signs of a serious condition.

Keep out of reach of children.

In case of eye exposure (flush eyes with water); or in case of accidental ingestion, seek medical help or contact a Poison Control Center right away.

Directions

-See important warnings under "When using this product"

-Adults & Children 2 years & over: use 1 tablespoon of solution for each quart of water or 1-1/2 teaspoons of solution for each pint of water

-add solution directly to cold water only in a hot steam vaporizer

-follow manufacturer's directions for using vaporizer

-breathe in medicated vapors

-may be repeated up to 3 times a day

-Children under 2 years: do not use

Other information

-Close container tightly and store at room temperature away from heat

Inactive Ingredients

dimethicone, eucalyptus globulus (eucalyptus oil) leaf oil, laureth-7, menthol, myristica fragrans (nutmeg) kernel oil, poloxamer 124, SD alcohol 40-B, thuja occidentalis (cedar leaf) oil

Directions

-See important warnings under "When using this product"
-Adults & Children 2 years & over: use 1 tablespoon of solution for each quart of water or 1-1/2 teaspoons of solution for each pint of water
-add solution directly to cold water only in a hot steam vaporizer
-follow manufacturer's directions for using vaporizer
-breathe in medicated vapors
-may be repeated up to 3 times a day
-Children under 2 years: do not use